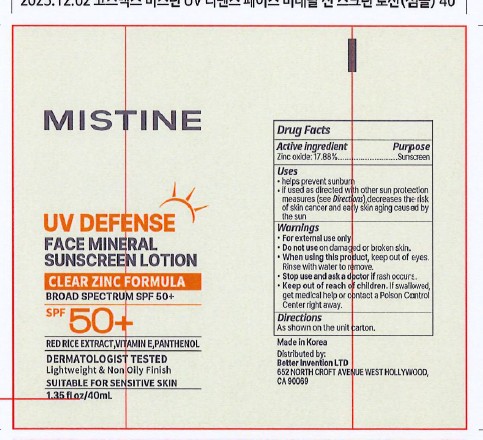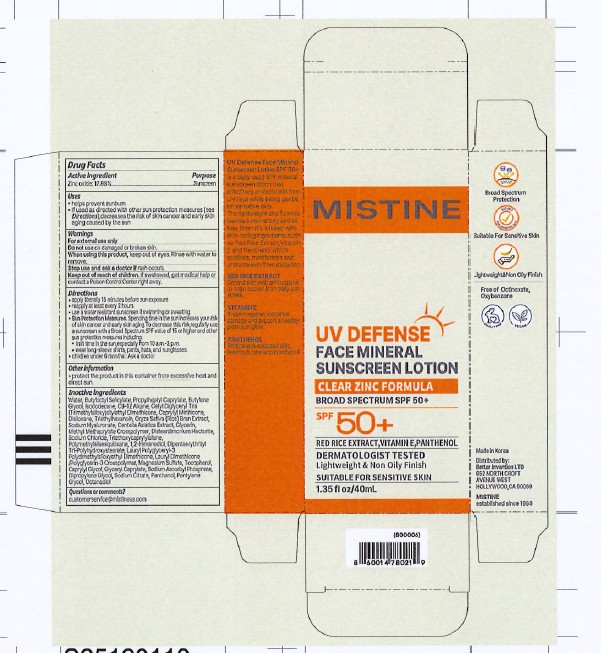 DRUG LABEL: UV DEFENSE FACE MINERAL SPF 50
NDC: 87458-003 | Form: LOTION
Manufacturer: BETTER INVENTION LTD
Category: otc | Type: HUMAN OTC DRUG LABEL
Date: 20260226

ACTIVE INGREDIENTS: ZINC OXIDE 17.88 mg/100 mL
INACTIVE INGREDIENTS: ORYZA SATIVA (RICE) BRAN; SODIUM HYALURONATE; CETYL DIGLYCERYL TRIS(TRIMETHYLSILOXY)SILYLETHYL DIMETHICONE (950 MM2/S); LAURYL POLYGLYCERYL-3 POLYDIMETHYLSILOXYETHYL DIMETHICONE (4000 MPA.S); SODIUM CITRATE; CENTELLA ASIATICA TRITERPENOIDS; SODIUM CHLORIDE; PROPYLHEPTYL CAPRYLATE; C9-12 ALKANE; GLYCERYL CAPRYLATE; SODIUM ASCORBYL PHOSPHATE; WATER; ISODODECANE; DISILOXANE; DIPENTAERYTHRITYL TRI-POLYHYDROXYSTEARATE; MAGNESIUM SULFATE; CAPRYLYL METHICONE; TRIETHYLHEXANOIN; DISTEARDIMONIUM HECTORITE; 1,2-HEXANEDIOL; POLYMETHYLSILSESQUIOXANE (4.5 MICRONS); BUTYLOCTYL SALICYLATE; TRIETHOXYCAPRYLYLSILANE; CAPRYLYL GLYCOL; BUTYLENE GLYCOL; TOCOPHEROL; PANTHENOL; PENTYLENE GLYCOL; DIPROPYLENE GLYCOL; OCTANEDIOL; GLYCERIN

MISTINE UV DEFENSE FACE MINERAL SUNSCREEN LOTION SPF 50+

Active Ingredient

Zinc oxide 17.88%

Purpose

Sunscreen

USES

- help prevent sunburn
- If used as directed with other sun protection measures (see Directions), decreases the risk of skin cancer and early skin aging caused by the sun.

Warnings

For external use only

Do not use on damaged or broken skin

When using this product, keep out of eyes. Rinse with water to remove.

Stop use and ask a doctor if rash occurs.

Keep out of reach of children. If swallowed, get medical help or contact a Poison Control Center right away.

DIRECTIONS

- apply liberally 15 minutes before sun exposure
- reapply at least every 2 hours
- use a water resistant sunscreen if swimming or sweating
- Sun Protection Measures. Spending time in the sun increases your risk of skin cancer and early skin aging. To decrease thi risk, regularly use a sunscreen with a Broad Spectrum SPF value of 15 or higher and other sun protection measures including:
- limit time in the sun, especially from 10 a.m. - 2 p.m.
- wear long-sleeve shirts, pants, hats, and sunglasses.
- children under 6 months: Ask a doctor

Inactive ingredients

water, butyloctyl salicylate, propylheptyl caprylate, butylene glycol, isododecane, C9-12 alkane, cetyl diglyceryl tris(trimethylsiloxy)silylethyl dimethicone, caprylyl methicone, disiloxane, triethylhexanoin, glycerin, methyl methacrylate crosspolymer, disteardimonium hectorite, sodium chloride, triethoxycaprylylsilane, polymethylsilsesquioxane, 1,2-hexanediol, dipentaerythrityl tri-polyhydroxystearate, lauryl polyglyceryl-3 polydimethylsiloxyethyl dimethicone, lauryl dimethicone/polyglycerin-3 crosspolymer, magnesium sulfate, tocopherol, caprylyl glycol, glyceryl caprylate, oryza sativa (rice) bran extract, sodium ascorbyl phosphate, dipropylene glycol, sodium hyaluronate, sodium citrate, panthenol, centella asiatica extract, pentylene glycol, octanediol.

OTHER INFORMATION

- protect the product in this container from excessive heat and direct sun.

QUESTIONS or COMMENTS?

customerservice@mistineus.com